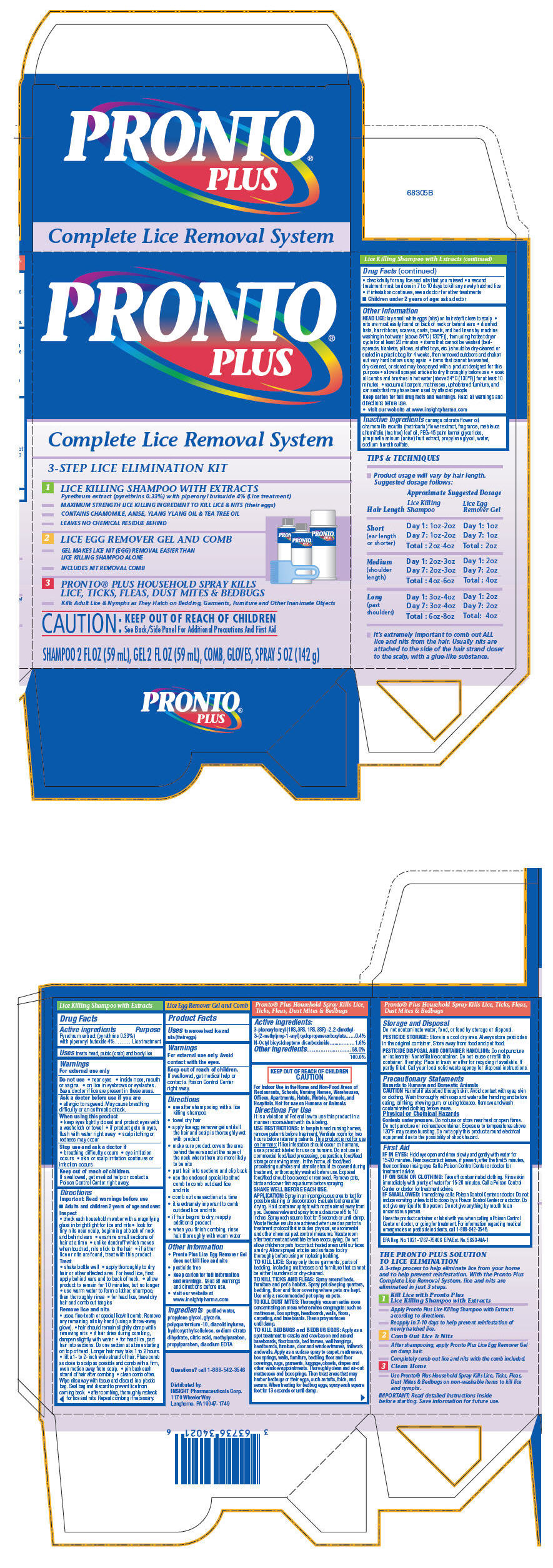 DRUG LABEL: Pronto Plus 
NDC: 63736-210 | Form: SHAMPOO
Manufacturer: Insight Pharmaceuticals LLC
Category: otc | Type: HUMAN OTC DRUG LABEL
Date: 20110120

ACTIVE INGREDIENTS: Pyrethrum Extract 0.0033 mL/1 mL; Piperonyl Butoxide 0.04 mL/1 mL
INACTIVE INGREDIENTS: Water; Cananga Oil; Chamomile; Tea Tree Oil; Pimpinella Anisum; Propylene Glycol; Sodium Laureth Sulfate

PRONTO®
PLUS

Lice Killing Shampoo with Extracts

Drug Facts

Active ingredients

Pyrethrum extract (pyrethrins 0.33%) with piperonyl butoxide 4%

Purpose

Lice treatment

Uses

treats head, pubic (crab) and body lice

Warnings

For external use only

Do not use

- near eyes
- inside nose, mouth or vagina
- on lice in eyebrows or eyelashes. See a doctor if lice are present in these areas.

Ask a doctor before use if you are

- allergic to ragweed. May cause breathing difficulty or an asthmatic attack.

When using this product

- keep eyes tightly closed and protect eyes with a washcloth or towel
- if product gets in eyes, flush with water right away
- scalp itching or redness may occur

Stop use and ask a doctor if

- breathing difficulty occurs
- eye irritation occurs
- skin or scalp irritation continues or infection occurs

Keep out of reach of children.

- If swallowed, get medical help or contact a Poison Control Center right away.

Directions

Important: Read warnings before use.

- Adults and children 2 years of age and over:
  Inspect
  - check each household member with a magnifying glass in bright light for lice and nits
  - look for tiny nits near scalp, beginning at back of neck and behind ears
  - examine small sections of hair at a time
  - unlike dandruff which moves when touched, nits stick to the hair
  - if either lice or nits are found, treat with this product
  Treat
  - shake bottle well
  - apply thoroughly to dry hair or other affected area. For head lice, first apply behind ears and to back of neck.
  - allow product to remain for 10 minutes, but no longer
  - use warm water to form a lather, shampoo, then thoroughly rinse
  - for head lice, towel dry hair and comb out tangles
  Remove lice and nits
  - use a fine-tooth or special lice/nit comb. Remove any remaining nits by hand (using a throw-away glove).
  - hair should remain slightly damp while removing nits
  - if hair dries during combing, dampen slightly with water
  - for head lice, part hair into sections. Do one section at a time starting on top of head. Longer hair may take 1 to 2 hours.
  - lift a 1- to 2- inch wide strand of hair. Place comb as close to scalp as possible and comb with a firm, even motion away from scalp.
  - pin back each strand of hair after combing
  - clean comb often. Wipe nits away with tissue and discard in a plastic bag. Seal bag and discard to prevent lice from coming back.
  - after combing, thoroughly recheck for lice and nits. Repeat combing if necessary.
  - check daily for any lice and nits that you missed
  - a second treatment must be done in 7 to 10 days to kill any newly hatched lice
  - if infestation continues, see a doctor for other treatments
- Children under 2 years of age: ask a doctor

Other Information

HEAD LICE: lay small white eggs (nits) on hair shaft close to scalp

- nits are most easily found on back of neck or behind ears
- disinfect hats, hair ribbons, scarves, coats, towels, and bed linens by machine washing in hot water [above 54°C (130°F)], then using hottest dryer cycle for at least 20 minutes
- items that cannot be washed (bedspreads, blankets, pillows, stuffed toys, etc.) should be dry-cleaned or sealed in a plastic bag for 4 weeks, then removed outdoors and shaken out very hard before using again
- items that cannot be washed, dry-cleaned, or stored may be sprayed with a product designed for this purpose
- allow all sprayed articles to dry thoroughly before use
- soak all combs and brushes in hot water [above 54°C (130°F)] for at least 10 minutes
- vacuum all carpets, mattresses, upholstered furniture, and car seats that may have been used by affected people

Keep carton for full drug facts and warnings. Read all warnings and directions before use.

- visit our website at www.insightpharma.com

Inactive Ingredients

cananga odorata flower oil, chamomilla recutita (matricaria) flower extract, fragrance, melaleuca alternifolia (tea tree) leaf oil, PEG-45 palm kernel glycerides, pimpinella anisum (anise) fruit extract, propylene glycol, water, sodium laureth sulfate.

Questions?

call 1-888-542-3546

Distributed by:
INSIGHT Pharmaceuticals Corp.
1170 Wheeler Way
Langhorne, PA 19047-1749

PRINCIPAL DISPLAY PANEL - Kit Carton

PRONTO®
PLUS

Complete Lice Removal System

3-STEP LICE ELIMINATION KIT

1 LICE KILLING SHAMPOO WITH EXTRACTS
  Pyrethrum extract (pyrethrins 0.33%) with piperonyl butoxide 4% (Lice treatment)
- MAXIMUM STRENGTH LICE KILLING INGREDIENT TO KILL LICE & NITS (their eggs)
- CONTAINS CHAMOMILE, ANISE, YLANG YLANG OIL & TEA TREE OIL
- LEAVES NO CHEMICAL RESIDUE BEHIND
2 LICE EGG REMOVER GEL AND COMB
- GEL MAKES LICE NIT (EGG) REMOVAL EASIER THAN
  LICE KILLING SHAMPOO ALONE
- INCLUDES NIT REMOVAL COMB
3 PRONTO® PLUS HOUSEHOLD SPRAY KILLS
  LICE, TICKS, FLEAS, DUST MITES & BEDBUGS
- Kills Adult Lice & Nymphs as They Hatch on Bedding, Garments, Furniture and Other Inanimate Objects

CAUTION: KEEP OUT OF REACH OF CHILDREN
See Back/Side Panel For Additional Precautions And First Aid

SHAMPOO 2 FL OZ (59 mL), GEL 2 FL OZ (59 mL), COMB, GLOVES, SPRAY 5 OZ (142 g)